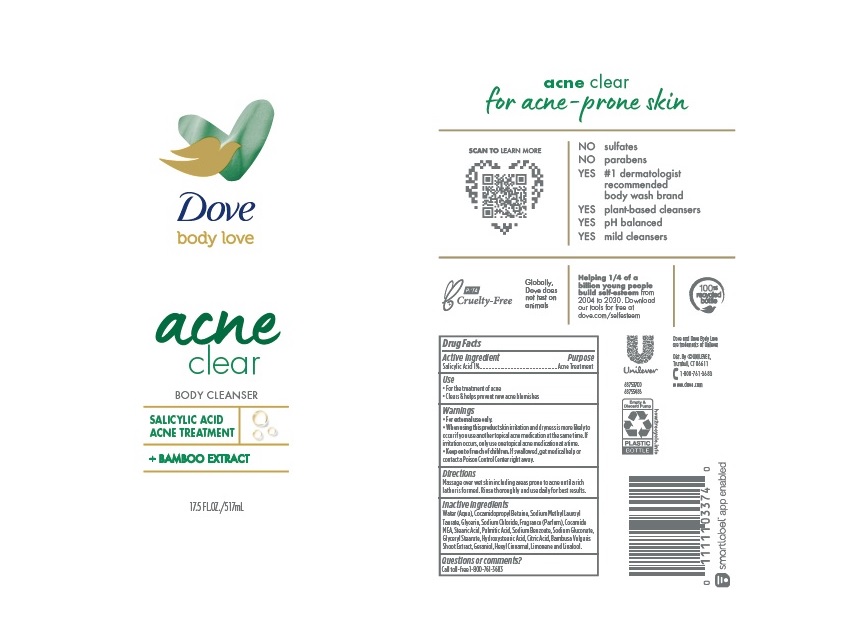 DRUG LABEL: Dove
NDC: 64942-2074 | Form: LIQUID
Manufacturer: CONOPCO Inc. d/b/a Unilever
Category: otc | Type: HUMAN OTC DRUG LABEL
Date: 20241107

ACTIVE INGREDIENTS: SALICYLIC ACID 1 g/100 mL
INACTIVE INGREDIENTS: WATER; GLYCERIN; SODIUM LAUROYL METHYL TAURATE; COCAMIDOPROPYL BETAINE; COCO MONOETHANOLAMIDE; SODIUM CHLORIDE; SODIUM GLUCONATE; SODIUM BENZOATE; GLYCERYL MONOSTEARATE; 12-HYDROXYSTEARIC ACID; STEARIC ACID; GERANIOL; PALMITIC ACID; .ALPHA.-HEXYLCINNAMALDEHYDE; LINALOOL, (+/-)-; LIMONENE, (+)-; BAMBUSA VULGARIS STEM; CITRIC ACID MONOHYDRATE

Dove Acne Clear Body Cleanser

Active ingredient

Salicylic Acid (1%)

Purpose

Acne Treatment

Uses

For the treatment of acne
Clears & helps prevent new acne blemishes

Warnings

For external use only
When using this product skin irritation and dryness is more likely to occur if you use another topical acne medication at the same time. If irritation occues, only use one topical acne medication at a time.

Keep out of reach of children
If swallowed, get medical help or contact a Poison Control Center right away.

Directions

Massage over wet skin including areas prone to acne until a rich lather is formed. Rinse thoroughly and use daily for best

Inactive ingredients

Water (Aqua), Cocamidopropyl Betaine, Sodium Methyl Lauroyl Taurate, Glycerin, Sodium Chloride, Fragrance (Parfum), Cocamide MEA, Stearic Acid, Palmitic Acid, Sodium Benzoate, Sodium Gluconate, Glyceryl Stearate, Hydroxystearic Acid, Citric Acid, Bambusa Vulgaris Shoot Extract, Geraniol, Hexyl Cinnamal, Limonene, Linalool.

Questions or comments?

Call toll-free 1-800-761-3683